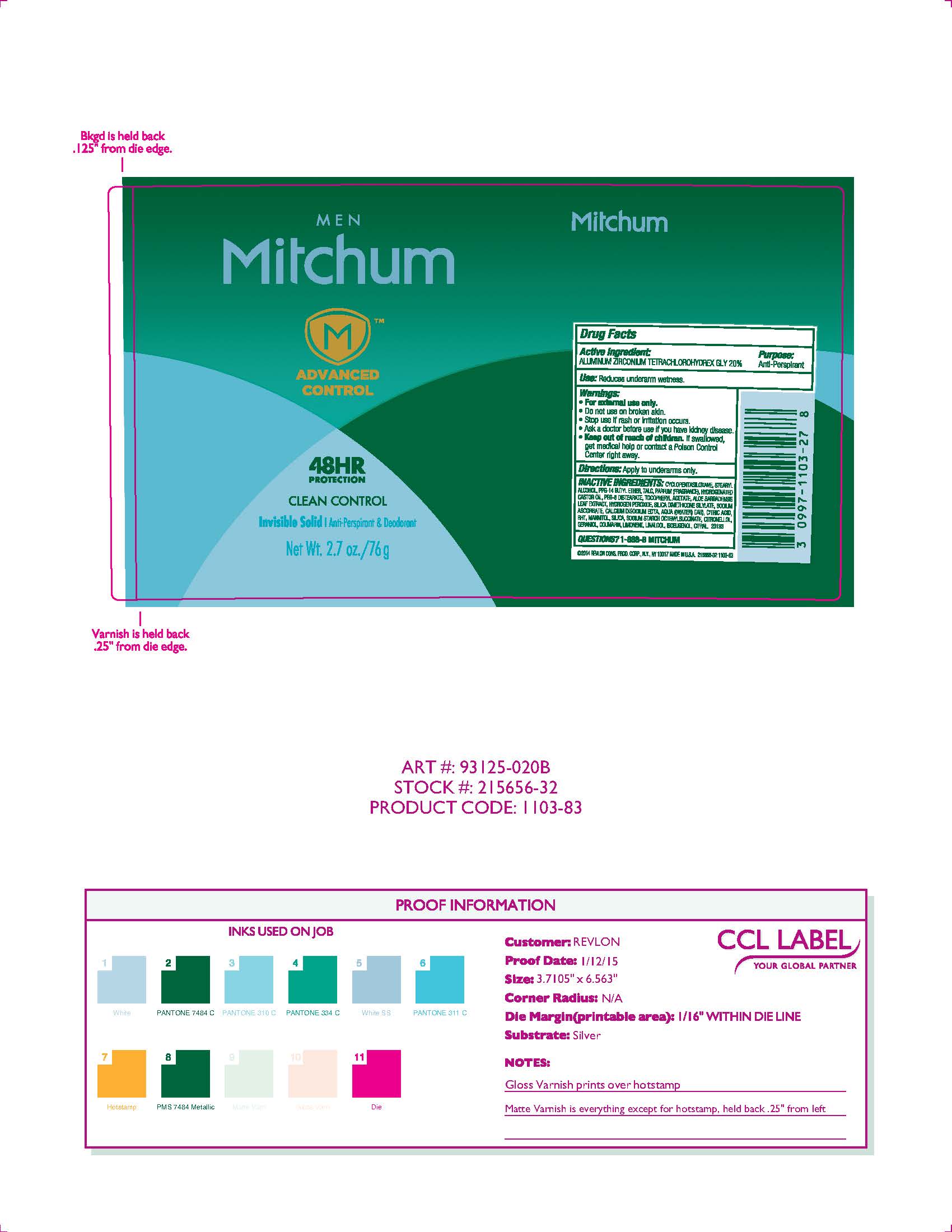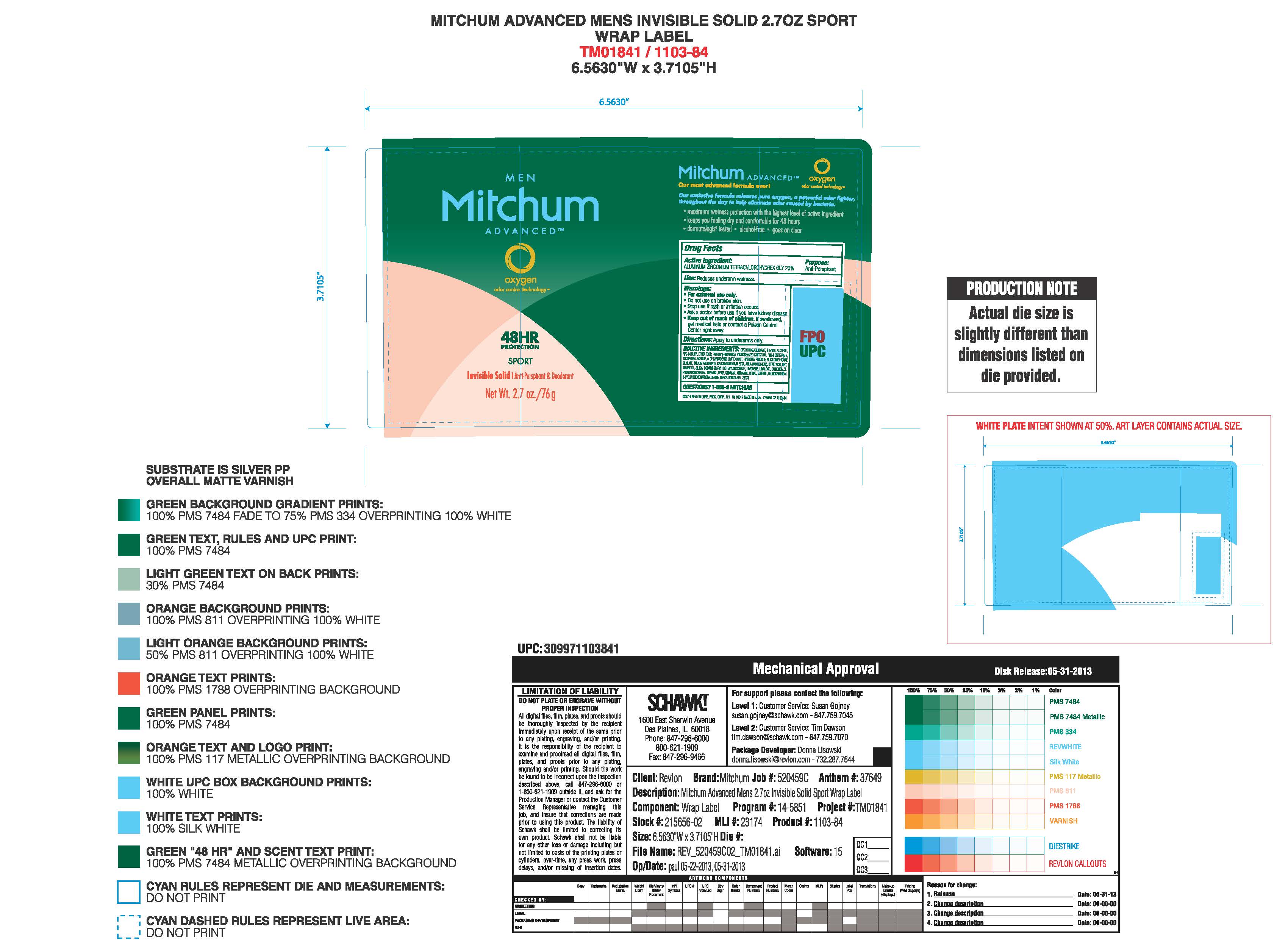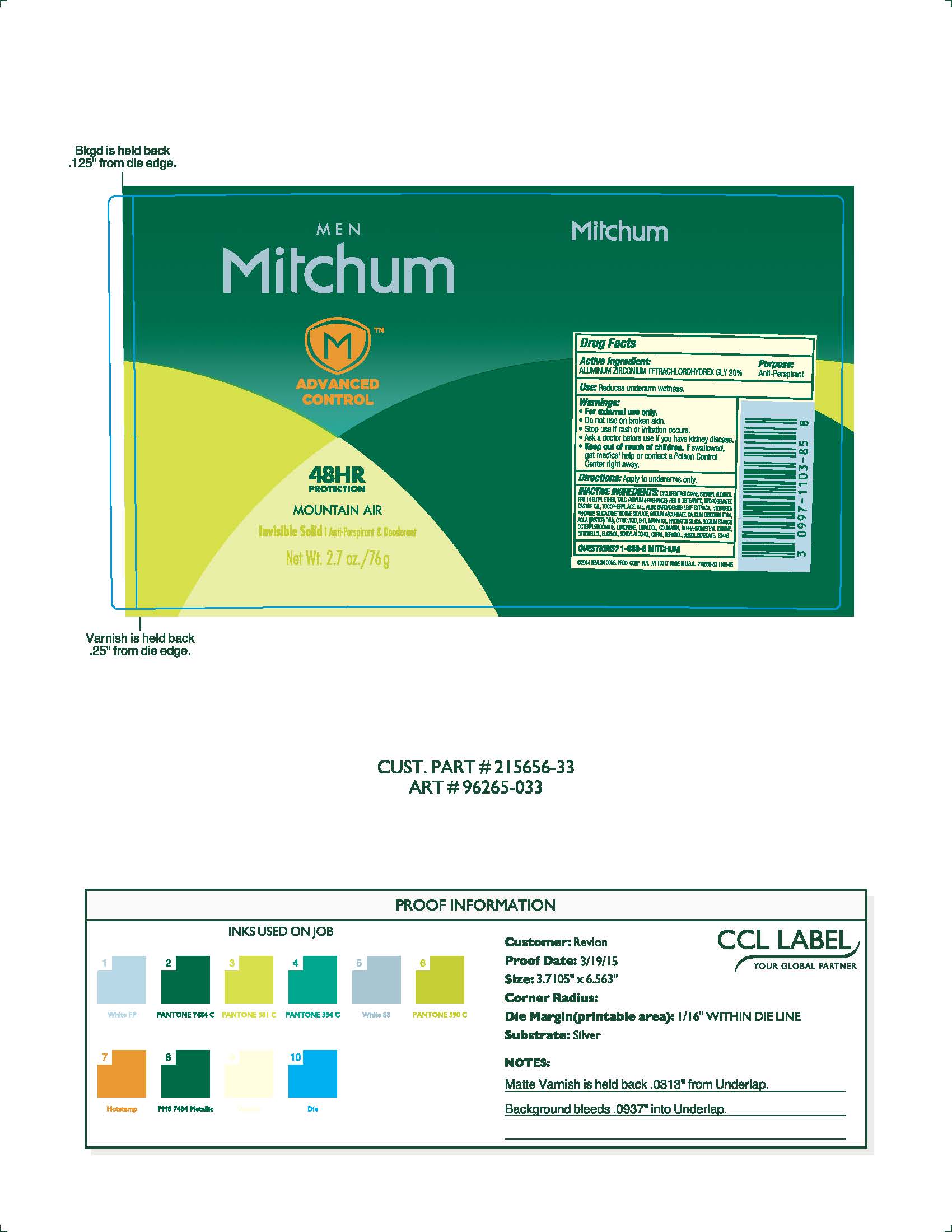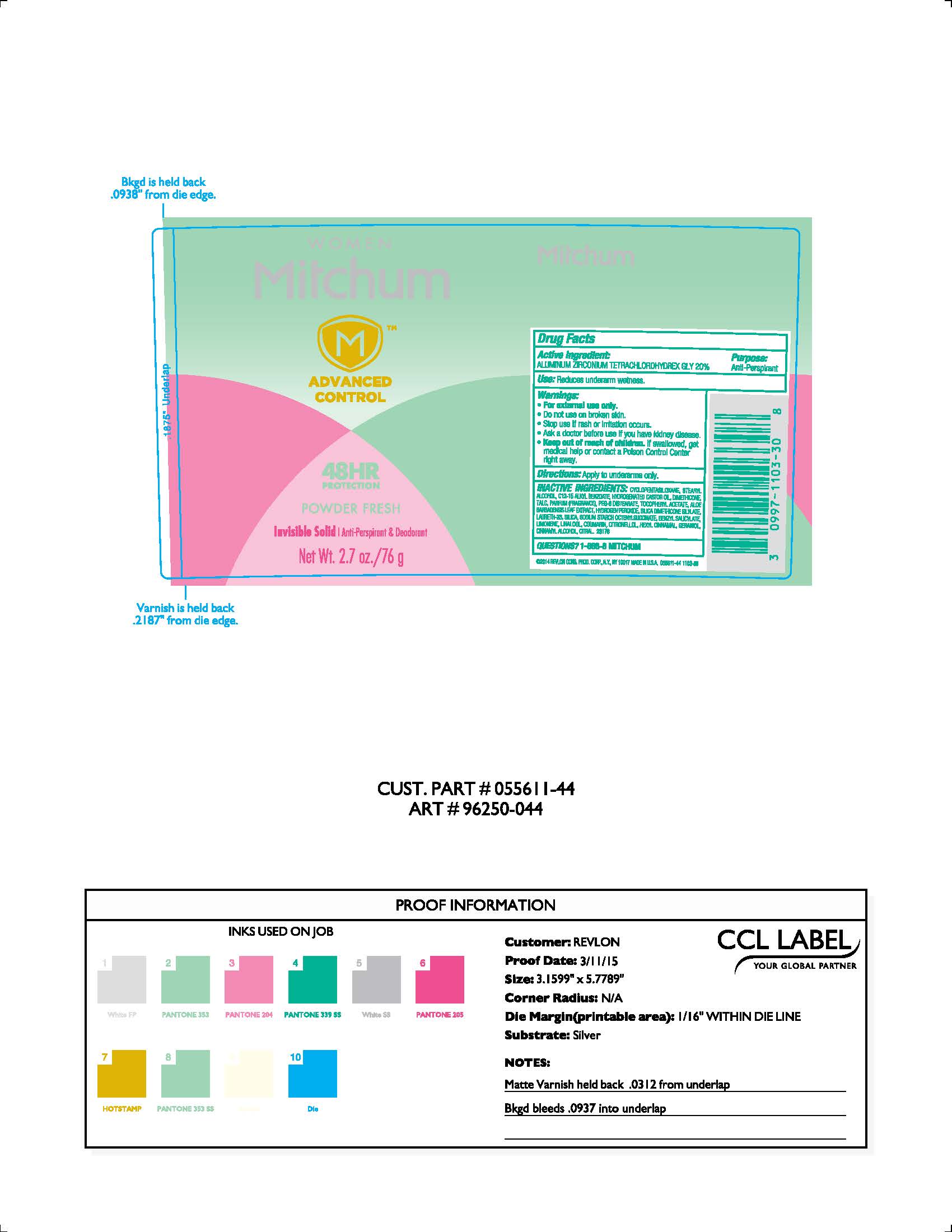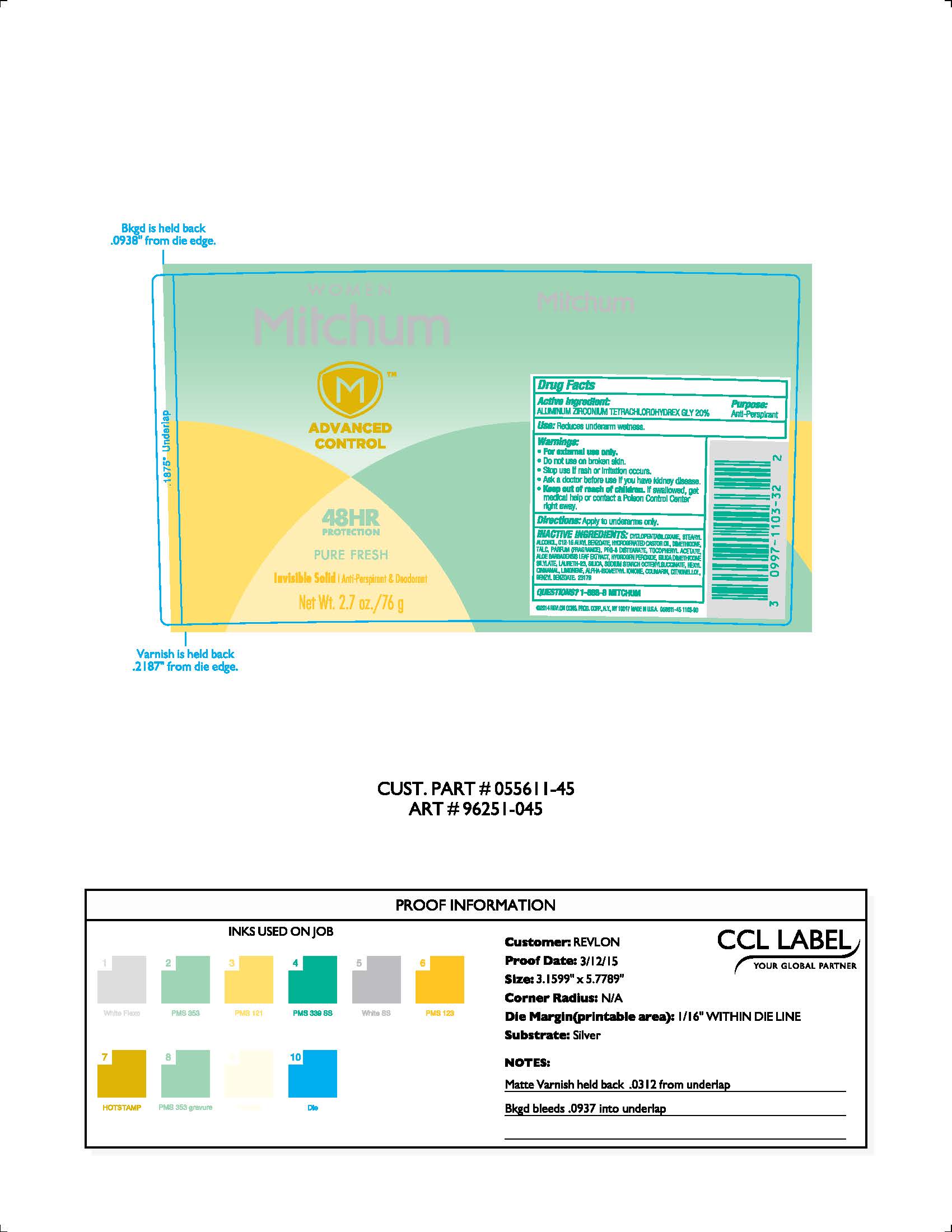 DRUG LABEL: Mitchum Advanced Control Solid
NDC: 10967-629 | Form: LIQUID
Manufacturer: Revlon Consumer Products Corp
Category: otc | Type: HUMAN OTC DRUG LABEL
Date: 20251229

ACTIVE INGREDIENTS: ALUMINUM ZIRCONIUM TETRACHLOROHYDREX GLY 0.2 g/1 mL
INACTIVE INGREDIENTS: CYCLOMETHICONE 5; STEARYL ALCOHOL; PPG-14 BUTYL ETHER; TALC; HYDROGENATED CASTOR OIL; PEG-8 DISTEARATE; .ALPHA.-TOCOPHEROL ACETATE; ALOE VERA LEAF; MANNITOL; .BETA.-CITRONELLOL, (R)-; GERANIOL; SILICON DIOXIDE; COUMARIN; HYDROGEN PEROXIDE; LIMONENE, (+/-)-; LINALOOL, (+/-)-; ISOEUGENOL; EDETATE CALCIUM DISODIUM ANHYDROUS; BUTYLATED HYDROXYTOLUENE; SODIUM ASCORBATE; CITRIC ACID MONOHYDRATE; CITRAL

Revlon Mitchum Advanced Control Solid

ACTIVE INGREDIENT

Aluminum Zirconium Tetrachlorohydrex Gly 20%

Purpose

Antiperspirant

Warnings:

For external use only.

Do not use on broken skin

Ask a doctor before use if you have kidney disease

Stop use if rash or irriation occurs

KEEP OUT OF REACH OF CHILDREN

If swallowed, get medical help or contact a Poison Control Center right away.

Inactive Ingredients

CYCLOPENTASILOXANE, STEARYL ALCOHOL, PPG-14 BUTYL ETHER, TALC, PARFUM (FRAGRANCE), HYDROGENATED CASTOR OIL, PEG-8 DISTEARATE, SODIUM STARCH OCTENYLSUCCINATE, TOCOPHERYL ACETATE, ALOE BARBADENSIS LEAF EXTRACT, MANNITOL, AQUA ((WATER) EAU), CITRONELLOL, GERANIOL, SILICA DIMETHICONE SILYLATE, SILICA, COUMARIN, HYDROGEN PEROXIDE, LIMONENE, LINALOOL, ISOEUGENOL, CALCIUM DISODIUM EDTA, BHT, SODIUM ASCORBATE, CITRIC ACID, CITRAL

INDICATIONS AND USAGE

Reduces underarm wetness